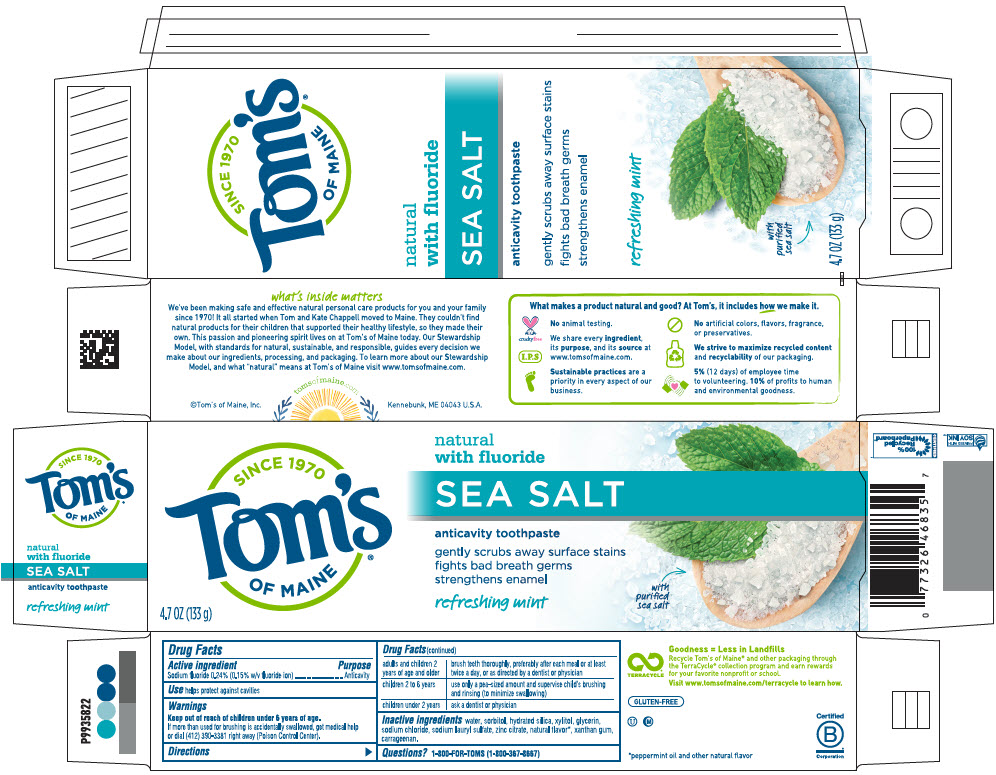 DRUG LABEL: Sea Salt Anticavity SALT47 
NDC: 51009-901 | Form: PASTE, DENTIFRICE
Manufacturer: Toms of Maine, Inc.
Category: otc | Type: HUMAN OTC DRUG LABEL
Date: 20190830

ACTIVE INGREDIENTS: Sodium Fluoride 0.0024 g/1 g
INACTIVE INGREDIENTS: Water; Sorbitol; Hydrated Silica; Xylitol; Glycerin; Sodium Chloride; Sodium Lauryl Sulfate; Zinc Citrate; Peppermint Oil; Xanthan Gum; Carrageenan

Sea Salt Anticavity Toothpaste SALT47
gently scrubs away surface stains / fights bad breath germs / strengthens enamel

Drug Facts

Active ingredient

Sodium fluoride 0.24% (0.15% w/v fluoride ion)

Purpose

Anticavity

Use

helps protect against cavities

Warnings

Keep out of reach of children under 6 years of age.

If more than used for brushing is accidentally swallowed, get medical help or dial (412) 390-3381 right away (Poison Control Center).

Directions

adults and children 2 years of age and older | brush teeth thoroughly, preferably after each meal or at least twice a day, or as directed by a dentist or physician
children 2 to 6 years | use only a pea-sized amount and supervise child's brushing and rinsing (to minimize swallowing)
children under 2 years | ask a dentist or physician

Inactive ingredients

water, sorbitol, hydrated silica, xylitol, glycerin, sodium chloride, sodium lauryl sulfate, zinc citrate, natural flavor [peppermint oil and other natural flavor] , xanthan gum, carrageenan.

Questions?

1-800-FOR-TOMS (1-800-367-8667)

PRINCIPAL DISPLAY PANEL - 133 g Tube Carton

4.7 OZ (133 g)

SINCE 1970
Tom's®
OF MAINE

natural
with fluoride

SEA SALT

anticavity toothpaste

gently scrubs away surface stains
fights bad breath germs
strengthens enamel

refreshing mint

with
purified
sea salt